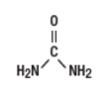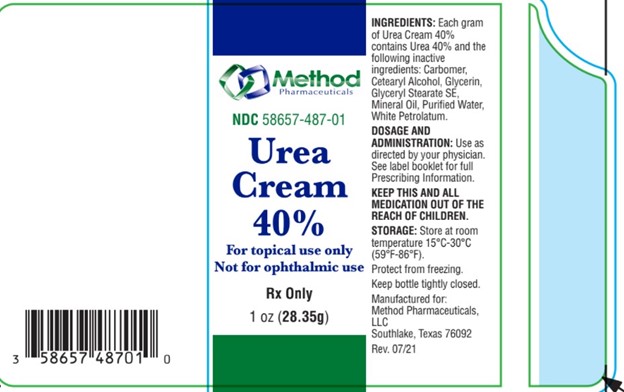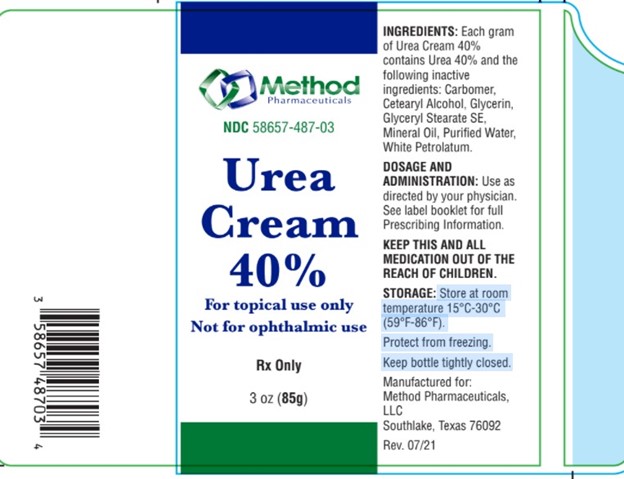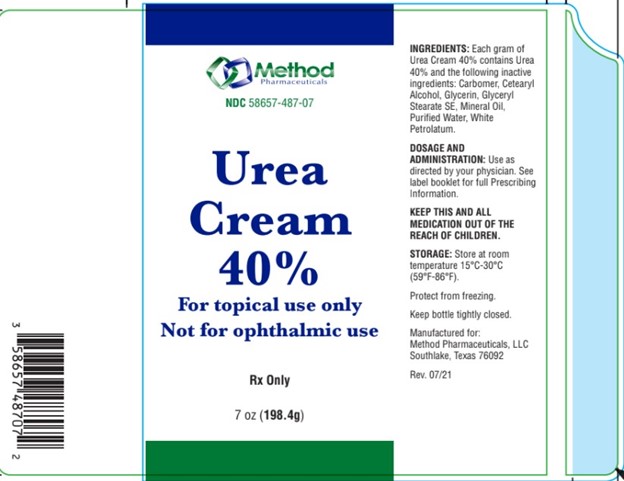 DRUG LABEL: Urea 40 Percent
NDC: 58657-487 | Form: CREAM
Manufacturer: Method Pharmaceuticals, LLC
Category: prescription | Type: HUMAN PRESCRIPTION DRUG LABEL
Date: 20260212

ACTIVE INGREDIENTS: UREA 400 mg/1 g
INACTIVE INGREDIENTS: GLYCERIN; CARBOMER HOMOPOLYMER, UNSPECIFIED TYPE; CETYL ALCOHOL; WHITE PETROLATUM; MINERAL OIL; WATER; GLYCERYL STEARATE SE

Urea 40 Percent Cream

DESCRIPTION:

INGREDIENTS: Each gram
of Urea Cream 40%
contains Urea 40% and the
following inactive
ingredients: Carbomer,
Cetearyl Alcohol, Glycerin,
Glyceryl Stearate SE,
Mineral Oil, Purified Water,
White Petrolatum.

CLINICAL PHARMACOLOGY:

Urea gently dissolves the intercellular matrix which results in loosening the horny layer of skin and shedding scaly skin at regular intervals, thereby softening hyperkeratotic areas of the skin.

Pharmacokinetics:

The mechanism of action of topically applied urea is not yet known.

INDICATIONS:

This product is useful for the treatment of hyperkeratotic conditions such as dry, rough skin, xerosis, ichthyosis, skin cracks and fissures, dermatitis, eczema, psoriasis, keratoses and calluses.

CONTRAINDICATIONS:

This product is contraindicated in persons with known or suspected hypersensitivity to any of the ingredients of the product.

WARNINGS:

FOR EXTERNAL USE ONLY. NOT FOR OPHTHALMIC USE. KEEP OUT OF REACH OF CHILDREN.

Avoid contact with eyes, lips and mucous membranes.

General:

This product is to be used as directed by a physician and should not be used to treat any condition other than that for which it was prescribed. If redness or irritation occurs, discontinue use and consult a physician.

Information for Patients:

Patients should discontinue the use of this product if the condition becomes worse or if a rash develops in the area being treated or elsewhere. Avoid contact with eyes, lips and mucous membranes.

Carcinogenesis, Mutagenesis and Impairment of Fertility:

Long-term animal studies for carcinogenic potential have not been performed on this product to date. Studies on reproduction and fertility also have not been performed.

Pregnancy:

Category C. Animal reproduction studies have not been conducted with this product. It is also not known whether this product can affect reproduction capacity or cause fetal harm when administered to a pregnant woman. This product should be used by a pregnant woman only if clearly needed or when potential benefits outweigh potential hazards to the fetus.

Nursing Mothers:

It is not known whether this drug is excreted in human milk. Because many drugs are excreted in human milk, caution should be exercised when this product is administered to a nursing woman.

ADVERSE REACTIONS:

Transient stinging, burning, itching or irritation may occur and normally disappear upon discontinuing the use of this product.

DOSAGE AND ADMINISTRATION:

Use as
directed by your physician.
See label booklet for full
Prescribing Information.

STORAGE:

Store at room
temperature 15°C-30°C
(59°F-86°F).
Protect from freezing.
Keep bottle tightly closed.

HOW SUPPLIED:

This product is supplied in the following size(s): 3 oz, 1 oz, and 7oz

To report a serious adverse event or obtain product information, call 877-250-3427

To report a serious adverse event, please contact Method Pharmaceuticals at (877) 250-3427; email at contact@methodpharm.com; or call FDA at (800) FDA-1088.

Manufactured for:
Method Pharmaceuticals, LLC Fort Worth, Texas 76118
Rev. 11/21